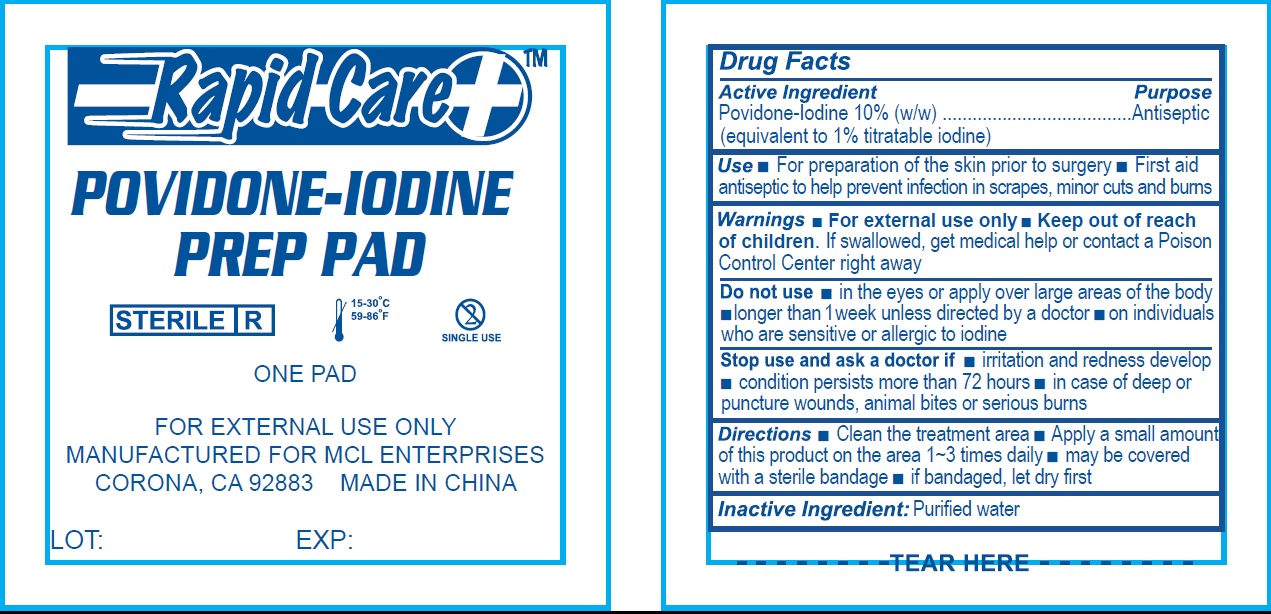 DRUG LABEL: Povidone Iodine Prep
NDC: 71622-003 | Form: PATCH
Manufacturer: MCL Enterprises
Category: otc | Type: HUMAN OTC DRUG LABEL
Date: 20171228

ACTIVE INGREDIENTS: POVIDONE-IODINE 100 mg/1 g
INACTIVE INGREDIENTS: WATER

Povidone-Iodine Prep Pad

Active Ingredient

Povidone-Iodine 10% (w/w) (equivalent to 1 % titratable iodine)

Purpose

Antiseptic

Use:

- For preparation of the skin prior to surgery
- First aid antiseptic to help prevent infection in scrapes, minor cuts and burns

Warnings:

- For external use only

Keep out of reach of children.

- If swallowed, get medical help or contact a Poison Control Center right away.

Do not use:

- in the eyes or apply over large areas of the body
- longer than 1 week unless directed by a doctor
- on individuals who are sensitive or allergic to iodine

Stop use and ask a doctor if:

- if irritation and redness develop.
- condition persists more than 72 hours
- in case of deep or puncture wounds, animal bites or serious burns

Directions:

- Clean the treatment area
- Apply a small amout of this product on the area 1~3 times daily
- may be covered with a sterile bandage
- if bandaged, let dry first

Inactive Ingredient:

Purified Water